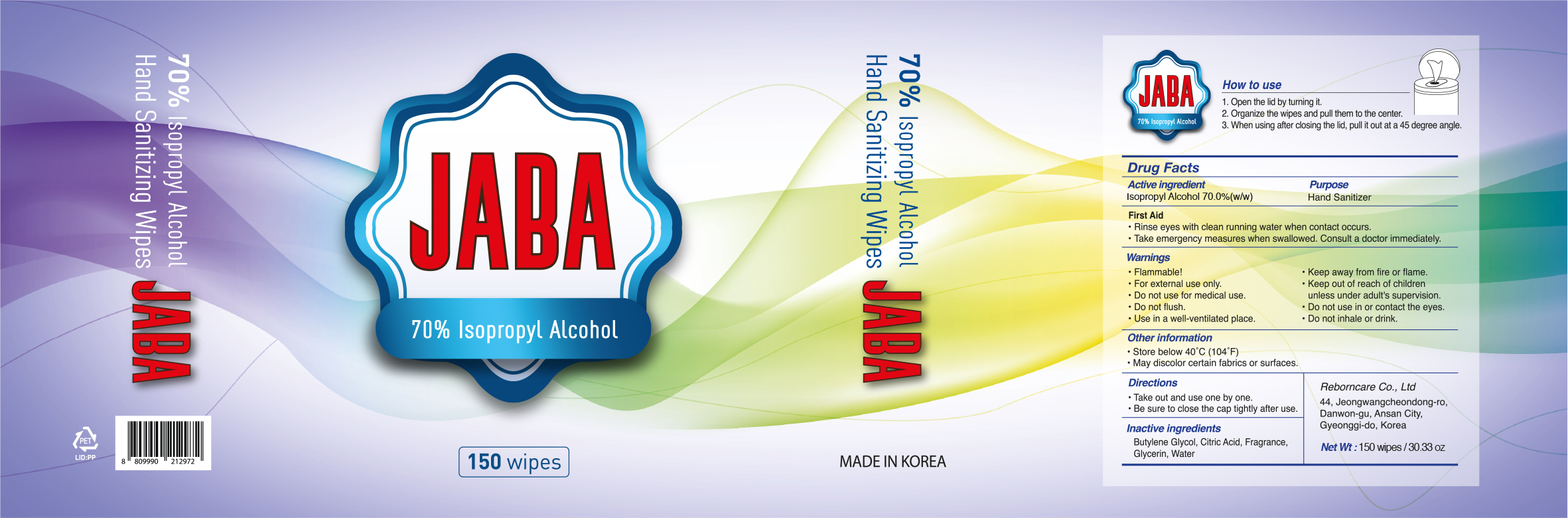 DRUG LABEL: Hand Sanitizing Wipes JABA
NDC: 79486-110 | Form: CLOTH
Manufacturer: Reborncare
Category: otc | Type: HUMAN OTC DRUG LABEL
Date: 20201201

ACTIVE INGREDIENTS: ISOPROPYL ALCOHOL 0.70 1/1 1
INACTIVE INGREDIENTS: Butylene Glycol; CITRIC ACID MONOHYDRATE; Glycerin; Water

ACTIVE INGREDIENT

Isopropyl Alcohol 70.0% (w/w)

INACTIVE INGREDIENT

Butylene Glycol, Citric Acid, Fragrance, Glycerin, Water

PURPOSE

Hand Sanitizer

WARNINGS

• Flammable!

• Keep away from fire or flame.

• For external use only.

• Keep out of reach of children unless under adult's supervision.

• Do not use for medical use.

• Do not flush.

• Do not use in or contact the eyes.

• Use in a well-ventilated place.

• Do not inhale or drink.

Keep out of reach of children unless under adult's supervision.

First Aid

• Rinse eyes with clean running water when contact occurs.
• Take emergency measures when swallowed. Consult a doctor immediately.

Directions

• Take out and use one by one.
• Be sure to close the cap tightly after use.

Other Information

• Store below 40˚C (104˚F)
• May discolor certain fabrics or surfaces.